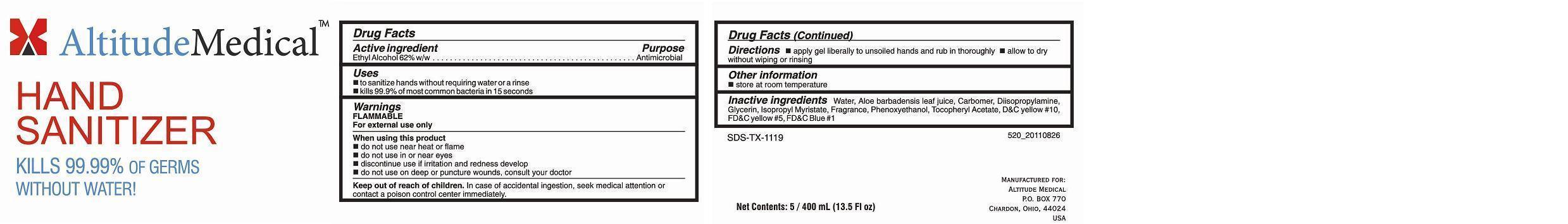 DRUG LABEL: AltitudeMedical HAND ANTIBACTERIAL
NDC: 69345-520 | Form: SOAP
Manufacturer: Altitude Medical Inc
Category: otc | Type: HUMAN OTC DRUG LABEL
Date: 20150122

ACTIVE INGREDIENTS: ALCOHOL 0.62 mL/1 mL
INACTIVE INGREDIENTS: WATER; CARBOMER HOMOPOLYMER TYPE C (ALLYL PENTAERYTHRITOL CROSSLINKED); GLYCERIN; ALOE VERA LEAF; ISOPROPYL MYRISTATE; PHENOXYETHANOL; .ALPHA.-TOCOPHEROL ACETATE; DIISOPROPYLAMINE

Drug Facts Active ingredient

Ethyl Alcohol 62 % w/w

Purpose

Antimicrobial

Keep out of reach of children

In case of accidental ingestion, seek medical attention or contact a poison control center immediately.

Uses

 to sanitize hands without requiring water or a rinse
 kills 99.9% of most common bacteria in 15 seconds

Warnings FLAMMABLE For external use only

When using this product

 do not use near heat or flame

 do not use in or around the eyes

 discontinue use if irritation and redness develop
 do not use on deep or punture wounds, consult your doctor

Directions

 apply gel liberally to unsoiled hands and rub in thoroughly  allow to dry without wiping or rinsing

Other information

 store at room temperature

Inactive ingredients:

Water, Aloe Barbadensies Leaf Juice, Carbomer, Diisopropylamine, Glycerin, Isopropyl Myristate, Fragrance, Phenoxyethanol, Tocopheryl Acetate, D&C yellow #10, FD&C yellow #5, FD&C Blue #1